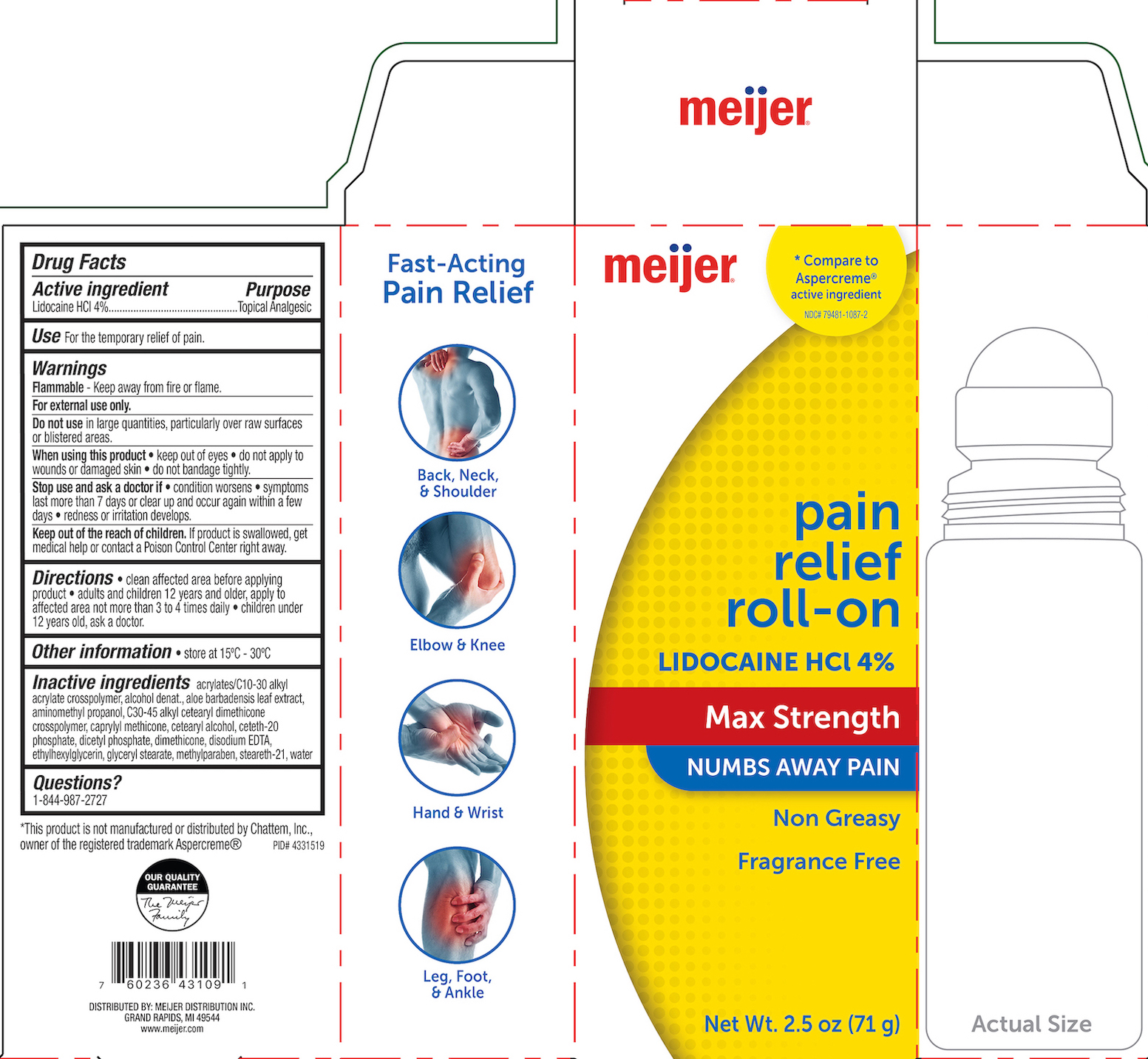 DRUG LABEL: Meijer Pain Relief
NDC: 79481-1087 | Form: GEL
Manufacturer: Meijer
Category: otc | Type: HUMAN OTC DRUG LABEL
Date: 20241220

ACTIVE INGREDIENTS: LIDOCAINE HYDROCHLORIDE 4 g/100 g
INACTIVE INGREDIENTS: DIMETHICONE 200; CARBOMER COPOLYMER TYPE B (ALLYL PENTAERYTHRITOL CROSSLINKED); ALCOHOL; AMINOMETHYLPROPANOL; C30-45 ALKYL CETEARYL DIMETHICONE CROSSPOLYMER; WATER; CETOSTEARYL ALCOHOL; CETETH-20 PHOSPHATE; ALOE VERA LEAF; DIHEXADECYL PHOSPHATE; CAPRYLYL TRISILOXANE; METHYLPARABEN; EDETATE DISODIUM; ETHYLHEXYLGLYCERIN; GLYCERYL MONOSTEARATE; STEARETH-21

Meijer Pain Relief Roll-on, Lidocaine HCl 4%

ACTIVE INGREDIENT

Lidocaine HCl 4%

PURPOSE

Topical Analgesic

INDICATIONS AND USAGE

For the temporary relief of pain.

WARNINGS

For external use only. Flammable--Do not use while smoking or near heat or flame. When using this product avoid contact with eyes, do not apply to wounds or damaged skin, and do not bandage tightly. Stop use and ask a doctor if condition worsens, if symptoms persist for more than 7 days or clear up and occur again within a few days, redness or irritation develops.

KEEP OUT OF REACH OF CHILDREN

If swallowed, get medical help or contact a Poison Control Center right away.

DOSAGE AND ADMINISTRATION

Clean affected area before applying product. Adults and children 12 years of age and older, apply to the affected area not more than 3 to 4 times daily. Children under 12 years old ask a doctor.

INACTIVE INGREDIENT

Acrylates/C10-30 alkyl acrylate crosspolymer, alcohol denat., aloe barbadensis leaf extract, aminomethyl propanol, C30-45 alkyl cetearyl dimehticone crosspolymer, carpylyl methicone, cetearyl alcohol, ceteth-20 phosphate, dicetyl phosphate, dimethicone, disodium EDTA, ethylhexylglycerin, glyceryl stearate, methylparaben, steareth-21, water.